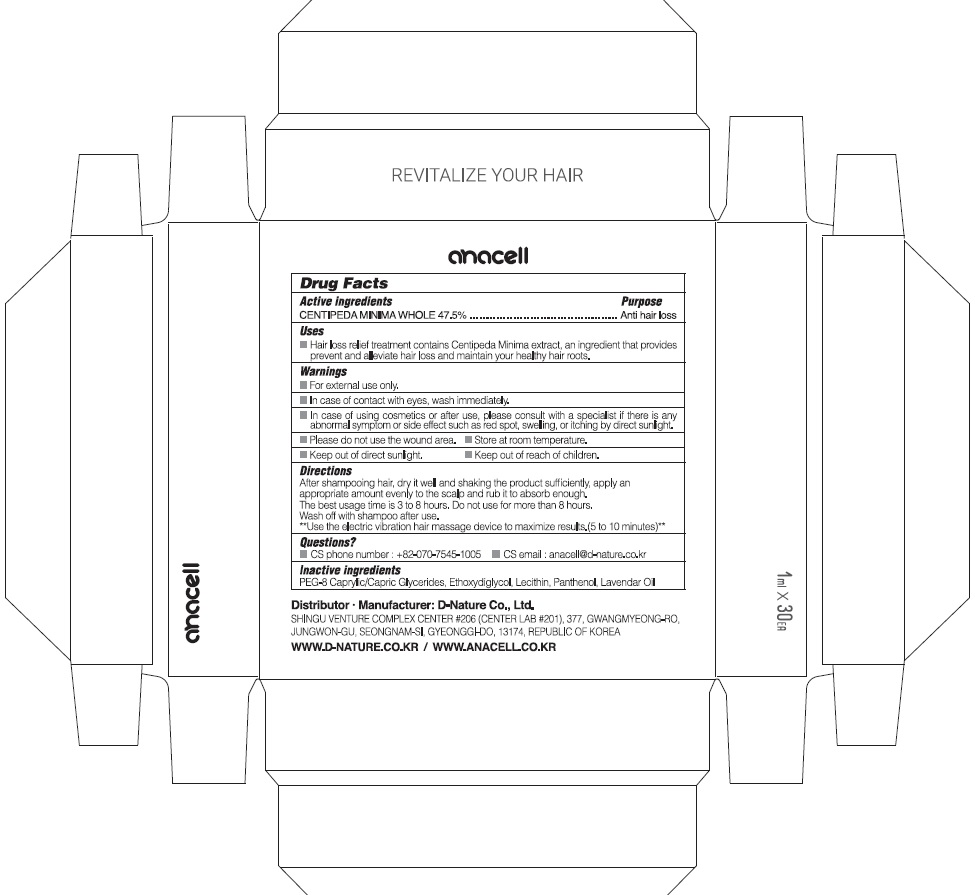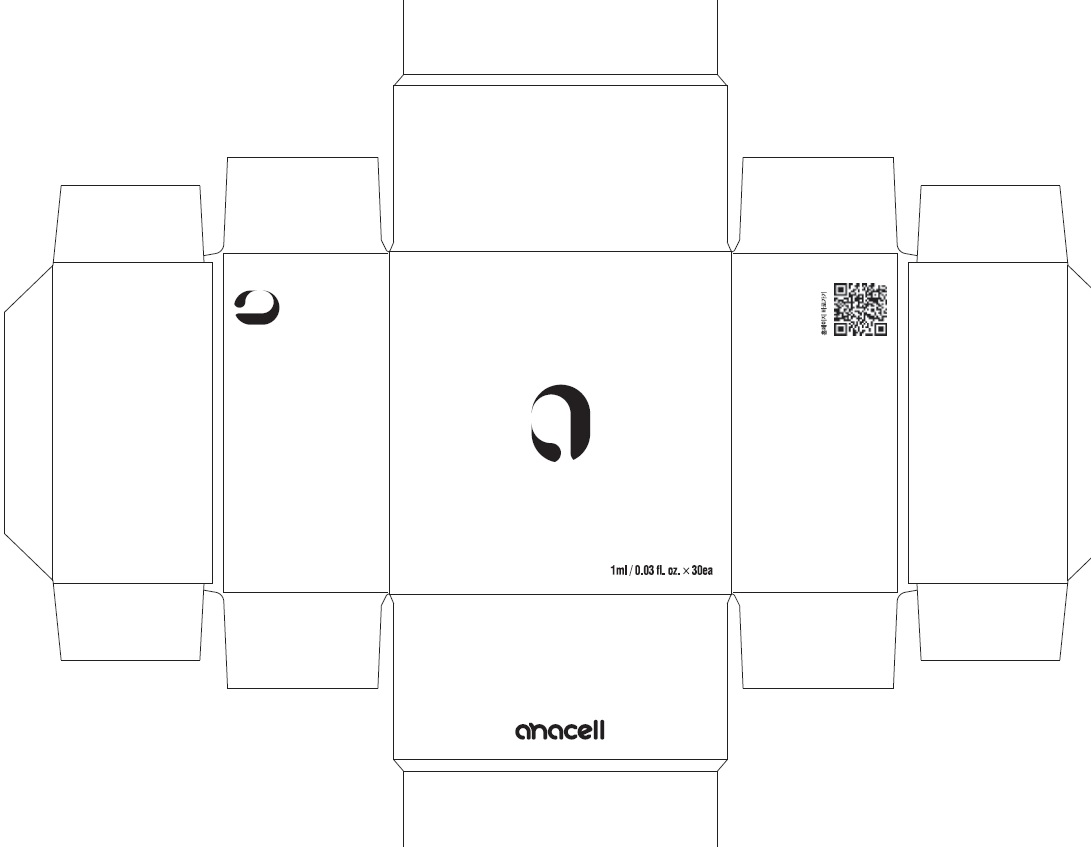 DRUG LABEL: ANACELL
NDC: 81823-010 | Form: LIQUID
Manufacturer: D-Nature Co., Ltd.
Category: otc | Type: HUMAN OTC DRUG LABEL
Date: 20210706

ACTIVE INGREDIENTS: CENTIPEDA MINIMA WHOLE 47.5 g/100 mL
INACTIVE INGREDIENTS: CAPRYLOCAPROYL POLYOXYLGLYCERIDES 8; DIETHYLENE GLYCOL MONOETHYL ETHER; Panthenol; LAVENDER OIL

ACTIVE INGREDIENT

CENTIPEDA MINIMA WHOLE 47.5%

INACTIVE INGREDIENTS

PEG-8 Caprylic/Capric Glycerides, Ethoxydiglycol, Lecithin, Panthenol, Lavender Oil

PURPOSE

Anti hair loss

WARNINGS

For external use only.

In case of contact with eyes, wash immediately.
In case of using cosmetics or after use, please consult with a specialist if there is any abnormal symptom or side effect such as red spot, swelling, or itching by direct sunlight.
Please do not use the wound area.
Store at room temperature.
Keep out of direct sunlight.
Keep out of reach of children.

KEEP OUT OF REACH OF CHILDREN

Uses

■ Hair loss relief treatment contains Centipeda Minima extract, an ingredient that provides prevent and alleviate hair loss and maintain your healthy hair roots.

Directions

After shampooing hair, dry it well and shaking the product sufficiently, apply an appropriate amount evenly to the scalp and rub it to absorb enough.
The best usage time is 3 to 8 hours.
Do not use for more than 8 hours.
Wash off with shampoo after use.
**Use the electric vibration hair massage device to maximize results. (5 to 10 minutes)**

QUESTIONS

CS phone number : +82-070-7545-1005
CS email : anacell@d-nature.co.kr